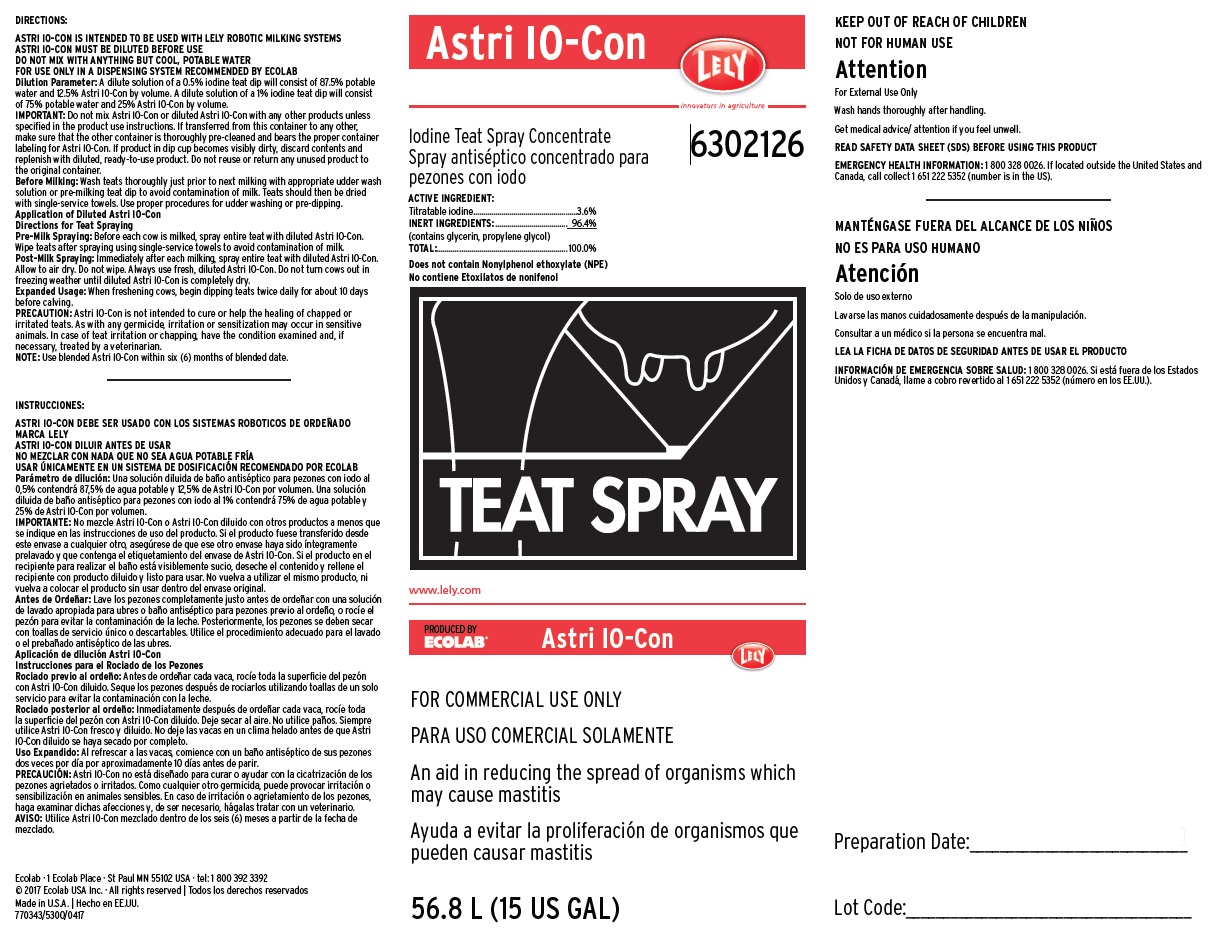 DRUG LABEL: Astri IO-Con
NDC: 47593-583 | Form: SOLUTION
Manufacturer: Ecolab Inc.
Category: animal | Type: OTC ANIMAL DRUG LABEL
Date: 20251024

ACTIVE INGREDIENTS: IODINE 36 mg/1 mL
INACTIVE INGREDIENTS: GLYCERIN; PROPYLENE GLYCOL; WATER

SAFE HANDLING WARNING

FOR COMMERCIAL USE ONLY

KEEP OUT OF REACH OF CHILDREN

NOT FOR HUMAN USE

Attention

For External Use Only

Wash hands thoroughly after handling.

Get medical advice/ attention if you feel unwell.

OTHER SAFETY INFORMATION

READ SAFETY DATA SHEET (SDS) BEFORE USING THIS PRODUCT
EMERGENCY HEALTH INFORMATION: 1 800 328 0026. If located outside the United States and Canada, call collect 1 651 222 5352 (number is in the US).

DIRECTIONS:

ASTRI IO-CON IS INTENDED TO BE USED WITH LELY ROBOTIC MILKING SYSTEMS

ASTRI IO-CON MUST BE DILUTED BEFORE USE

DO NOT MIX WITH ANYTHING BUT COOL, POTABLE WATER

FOR USE ONLY IN A DISPENSING SYSTEM RECOMMENDED BY ECOLAB

Dilution Parameter: A dilute solution of a 0.5% iodine teat dip will consist of 87.5% potable water and 12.5% Astri IO-Con by volume. A dilute solution of a 1% iodine teat dip will consist of 75% potable water and 25% Astri IO-Con by volume.

IMPORTANT: Do not mix Astri IO-Con or diluted Astri IO-Con with any other products unless specified in the product use instructions. If transferred from this container to any other, make sure that the other container is thoroughly pre-cleaned and bears the proper container labeling for Astri IO-Con. If product in dip cup becomes visibly dirty, discard contents and replenish with diluted, ready-to-use product. Do not reuse or return any unused product to the original container.

Before Milking: Wash teats thoroughly just prior to next milking with appropriate udder wash solution or pre-milking teat dip to avoid contamination of milk. Teats should then be dried with single-service towels. Use proper procedures for udder washing or pre-dipping.

Application of Diluted Astri IO-Con Directions for Teat Spraying

Pre-Milk Spraying: Before each cow is milked, spray entire teat with diluted Astri IO-Con. Wipe teats after spraying using single-service towels to avoid contamination of milk.

Post-Milk Spraying: Immediately after each milking, spray entire teat with diluted Astri IO-Con. Allow to air dry. Do not wipe. Always use fresh, diluted Astri IO-Con. Do not turn cows out in freezing weather until diluted Astri IO-Con is completely dry.

Expanded Usage: When freshening cows, begin dipping teats twice daily for about 10 days before calving.

PRECAUTION: Astri IO-Con is not intended to cure or help the healing of chapped or irritated teats. As with any germicide, irritation or sensitization may occur in sensitive animals. In case of teat irritation or chapping, have the condition examined and, if necessary, treated by a veterinarian.

NOTE: Use blended Astri IO-Con within six (6) months of blended date.

Principal Display Panel and Representative Label

Astri IO-Con

Iodine Teat Spra Concentrate

6302126

ACTIVE INGREDIENT:

Titratable iodine...............................................3.6%

INERT INGREDIENTS: ....................................96.4%

(contains glycerin, propylene glycol)

TOTAL:.........................................................100.0%

Does not contain Nonylphenol ethoxylate (NPE)

Teat Spray

www.lely.com

Produced by Ecolab Astri IO-Con

FOR COMMERCIAL USE ONLY

An aid in reducing the spread of organisms which may cause mastitis

56.8 L (15 US GAL)

Ecolab · 1 Ecolab Place · St Paul MN 55102 USA · tel: 1 800 392 3392

© 2017 Ecolab USA Inc. · All rights reserved

Made in U.S.A.

770343/5300/0417